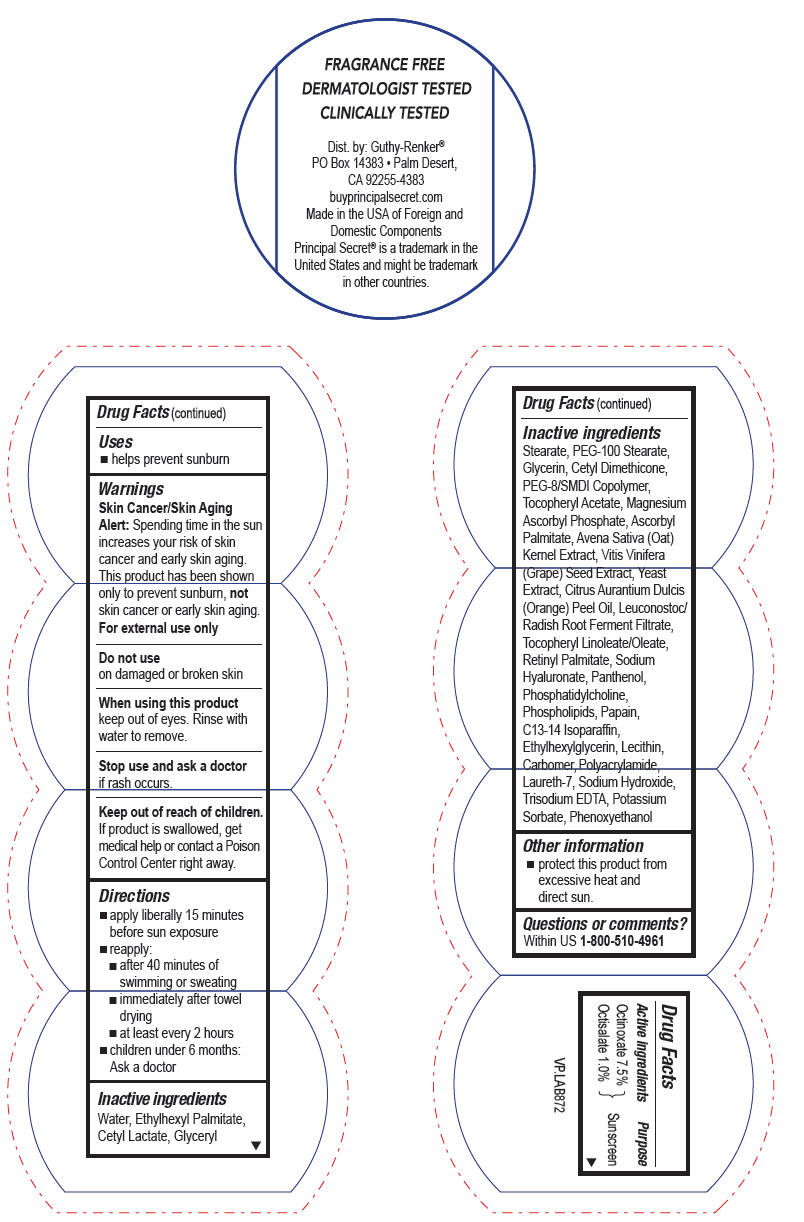 DRUG LABEL: Principal Secret Advanced with Hydrospheres Continuous Moisture SPF8
NDC: 70605-017 | Form: CREAM
Manufacturer: Guthy-Renker LLC
Category: otc | Type: HUMAN OTC DRUG LABEL
Date: 20240108

ACTIVE INGREDIENTS: Octinoxate 7.5 g/100 g; Octisalate 1 g/100 g
INACTIVE INGREDIENTS: ETHYLHEXYL PALMITATE; GLYCERYL MONOSTEARATE; PEG-100 STEARATE; Glycerin; VITAMIN A PALMITATE; PANTHENOL; HYALURONATE SODIUM; WINE GRAPE; .ALPHA.-TOCOPHEROL ACETATE, D-; ASCORBYL PALMITATE; PANTOTHENIC ACID; PHYTONADIONE; BERGAMOT OIL; LIMONENE, (+)-; AVENA SATIVA FLOWERING TOP; PAPAIN; LECITHIN, SOYBEAN; LAURETH-7; C13-14 ISOPARAFFIN; PEG-8 LAURATE; TROLAMINE; PHENOXYETHANOL; METHYLPARABEN; PROPYLPARABEN

Principal Secret® Advanced with Hydrospheres Continuous Moisture SPF8

Drug Facts

Active ingredients

Octinoxate 7.5%
Octisalate 1.0%

Purpose

Sunscreen

Uses

- helps prevent sunburn

Warnings

Skin Cancer/Skin Aging Alert

Spending time in the sun increases your risk of skin cancer and early skin aging. This product has been shown only to prevent sunburn, not skin cancer or early skin aging.

For external use only

Do not use

on damaged or broken skin

When using this product keep out of eyes. Rinse with water to remove.

Stop use and ask a doctor if rash occurs.

Keep out of reach of children. If product is swallowed, get medical help or contact a Poison Control Center right away.

Directions

- apply liberally 15 minutes before sun exposure
- reapply:
  - after 40 minutes of swimming or sweating
  - immediately after towel drying
  - at least every 2 hours
- children under 6 months: Ask a doctor

Inactive ingredients

Water, Ethylhexyl Palmitate, Cetyl Lactate, Glyceryl Stearate, PEG-100 Stearate, Glycerin, Cetyl Dimethicone, PEG-8/SMDI Copolymer, Tocopheryl Acetate, Magnesium Ascorbyl Phosphate, Ascorbyl Palmitate, Avena Sativa (Oat) Kernel Extract, Vitis Vinifera (Grape) Seed Extract, Yeast Extract, Citrus Aurantium Dulcis (Orange) Peel Oil, Leuconostoc/Radish Root Ferment Filtrate, Tocopheryl Linoleate/Oleate, Retinyl Palmitate, Sodium Hyaluronate, Panthenol, Phosphatidylcholine, Phospholipids, Papain, C13-14 Isoparaffin, Ethylhexylglycerin, Lecithin, Carbomer, Polyacrylamide, Laureth-7, Sodium Hydroxide, Trisodium EDTA, Potassium Sorbate, Phenoxyethanol

Other information

- protect this product from excessive heat and direct sun.

Questions or comments?

Within US 1-800-510-4961

Dist. by: Guthy-Renker®
PO Box 14383 • Palm Desert,
CA 92255-4383

PRINCIPAL DISPLAY PANEL - 57 g Jar Label

FRAGRANCE FREE
DERMATOLOGIST TESTED
CLINICALLY TESTED

Dist. by: Guthy-Renker®
PO Box 14383 • Palm Desert,
CA 92255-4383
buyprincipalsecret.com
Made in the USA of Foreign and
Domestic Components
Principal Secret® is a trademark in the
United States and might be trademark
in other countries.